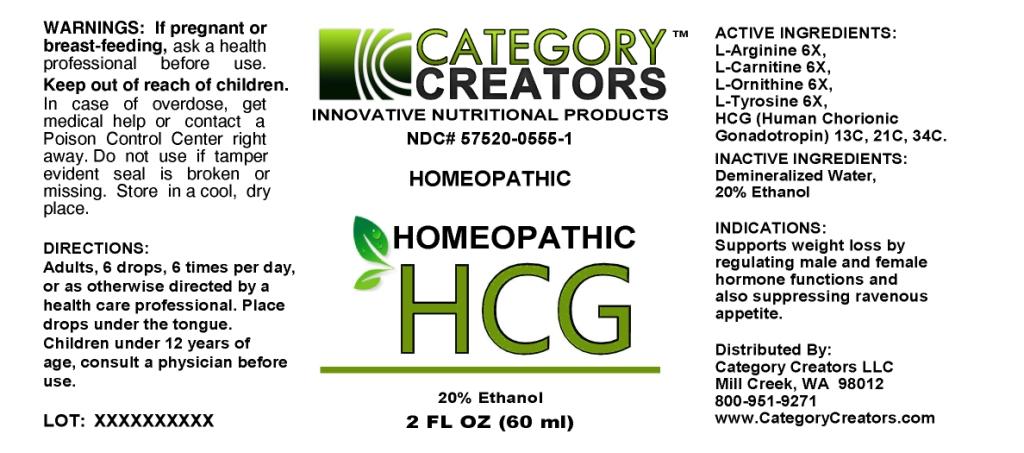 DRUG LABEL: Homeopathic HCG
NDC: 57520-0555 | Form: LIQUID
Manufacturer: Apotheca Company
Category: homeopathic | Type: HUMAN OTC DRUG LABEL
Date: 20100809

ACTIVE INGREDIENTS: ARGININE 6 [hp_X]/1 mL; LEVOCARNITINE HYDROCHLORIDE 6 [hp_X]/1 mL; ORNITHINE 6 mL/1 mL; TYROSINE 6 [hp_X]/1 mL; HUMAN CHORIONIC GONADOTROPIN 34 [hp_C]/1 mL
INACTIVE INGREDIENTS: WATER; ALCOHOL

Homeopathic HCG

ACTIVE INGREDIENT

ACTIVE INGREDIENTS: A-arginine 6X, L-carnitine 6X, L-ornithine 6X, L-tyrosine 6X, HCG(Human chorionic gonadotropin) 13C, 21C, 34C.

PURPOSE

INDICATIONS: Supports weight loss by regulating male and female hormone functions and also suppressing ravenous appetite.

WARNINGS

WARNINGS: If pregnant or breast-feeding, ask a health professional before use

Keep out of reach of children. In case of overdose, get medical help or contact a Poison Control Center right away.

Do not use if tamper evident seal is broken or missing. Store in a cool, dry place.

DOSAGE AND ADMINISTRATION

DIRECTIONS: Adults, 6 drops, 6 times per day, or as otherwise directed by a health care professional Place drops under the tongue. Children under 12 years of age, consult a physician before use.

INACTIVE INGREDIENTS: Demineralized water, 20% Ethanol.

QUESTIONS

Distributed by:

Category Creators LLC

Mill Creek, WA 98012

800-951-9271

www.CategoryCreators.com

PACKAGE LABEL

CATEGORY CREATORS

INNOVATIVE NUTRITIONAL PRODUCTS

NDC# 57520-0555-1

HOMEOPATHIC

HOMEOPATHIC HCG

2 FL OZ (60 ml)